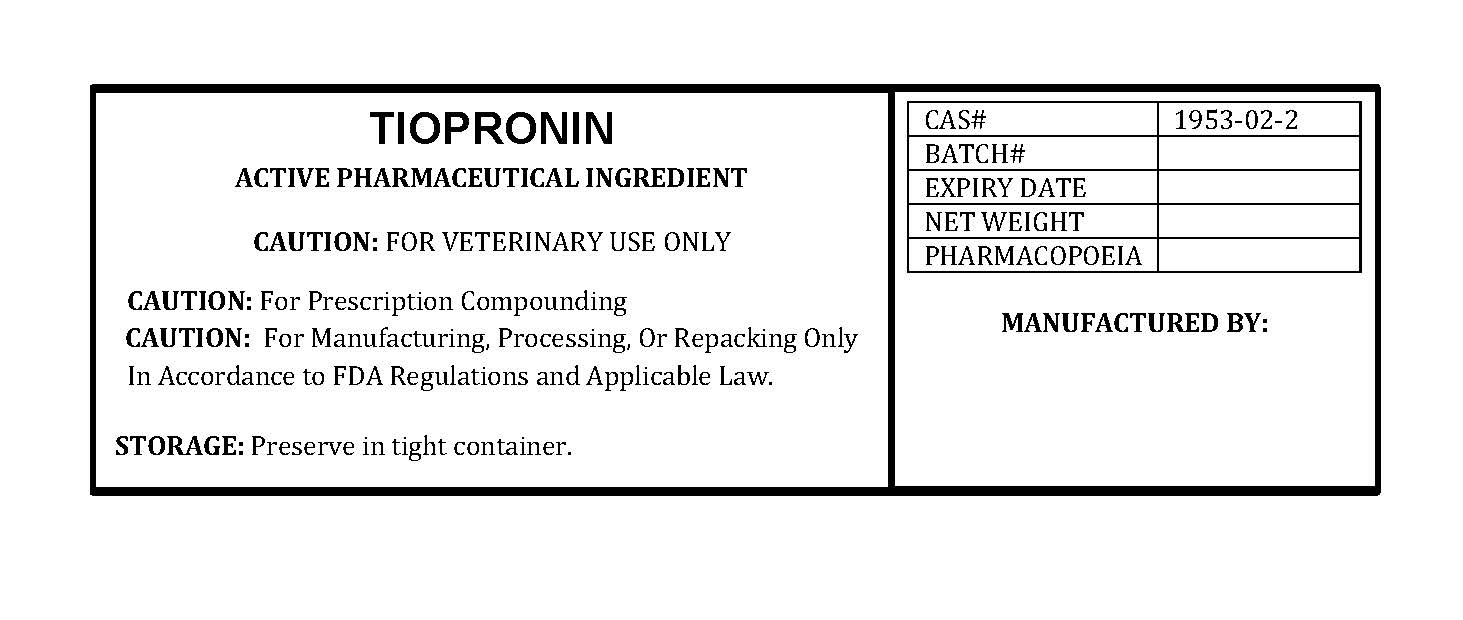 DRUG LABEL: TIOPRONIN
NDC: 86184-393 | Form: POWDER
Manufacturer: MAEDA INC
Category: other | Type: BULK INGREDIENT - ANIMAL DRUG
Date: 20251014

ACTIVE INGREDIENTS: TIOPRONIN 1 g/1 g

TIOPRONIN

PACKAGE LABEL

tioproninlabelfile.jpg